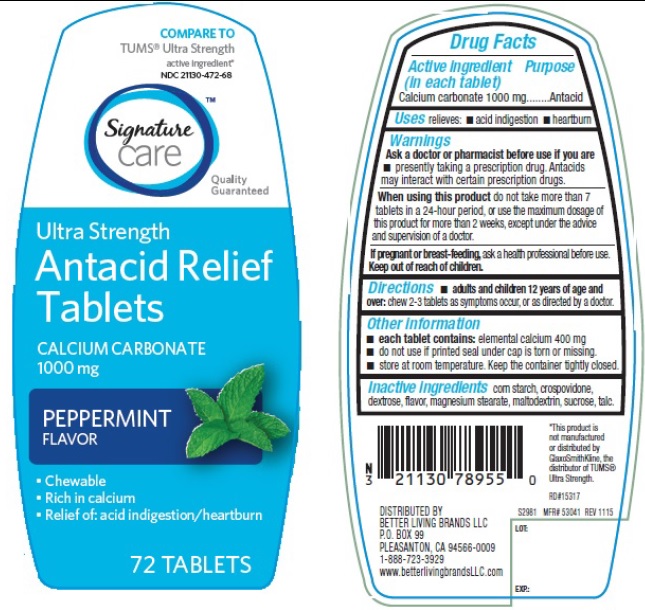 DRUG LABEL: Antacid Relief
NDC: 21130-472 | Form: TABLET, CHEWABLE
Manufacturer: Safeway
Category: otc | Type: HUMAN OTC DRUG LABEL
Date: 20160122

ACTIVE INGREDIENTS: CALCIUM CARBONATE 1000 mg/1 1
INACTIVE INGREDIENTS: STARCH, CORN; CROSPOVIDONE; DEXTROSE; MAGNESIUM STEARATE; MALTODEXTRIN; SUCROSE; TALC

Extra Strength Antacid Relief Tablets

Active ingredient (in each tablet)

Calcium carbonate 1000 mg

Purpose

Antacid

Uses

relieves: acid indigestion, heartburn

Warnings

Ask a doctor or pharmacist before use if you are

- presently taking a prescription drug. Antacids may interact with certain prescription drugs

When using this product

do not take more than 7 tablets in a 24-hour period, or use the maximum dosage of this product for more than 2 weeks, except under the advice and supervision of a doctor

Keep out of reach of children.

If pregnant or breast feeding, ask a health professional before use.

Directions

- adults and children 12 years of age and over: chew 2-3 tablets as symptoms occur, or as directed by a doctor.

Other information

- each tablet contains: elemental calcium 400 mg
- do not use if printed seal under cap is torn or missing
- store at room temperature. keep the container tightly closed.

Inactive ingredients

Corn starch, crospovidone, dextrose, flavor, magnesium stearate, maltodextrin, sucrose, talc

PDP

Compare to the TUMS Ultra strength active ingredient

Ultra strength

Antacid Relief Tablets

Calcium Carbonate 1000 mg

Peppermint Flavor

Chewable

Rich in calcium

Relief of: acid indigestion/heartburn

72 tablets